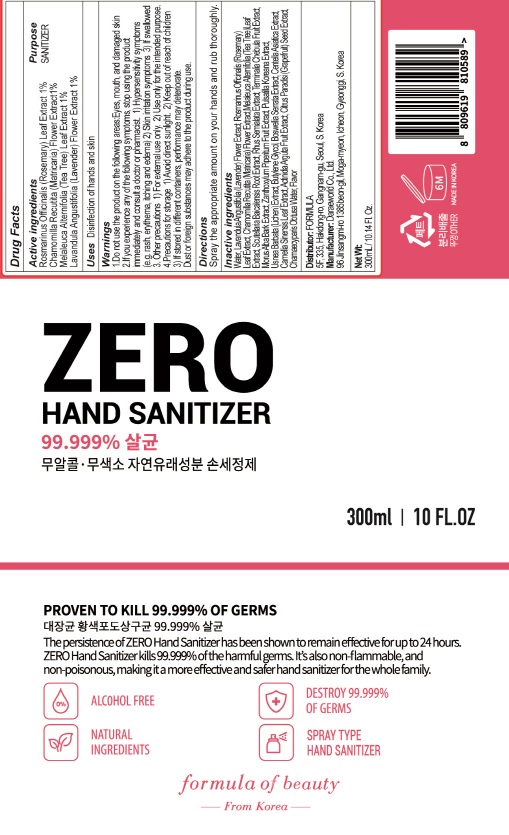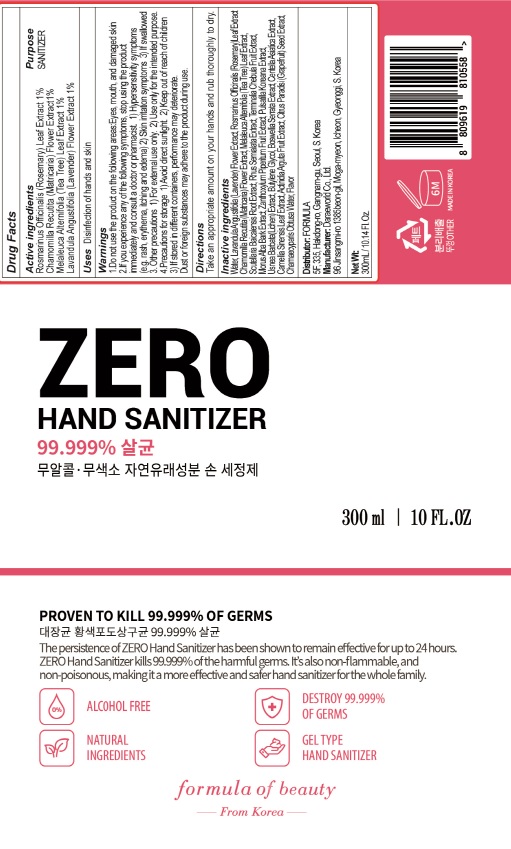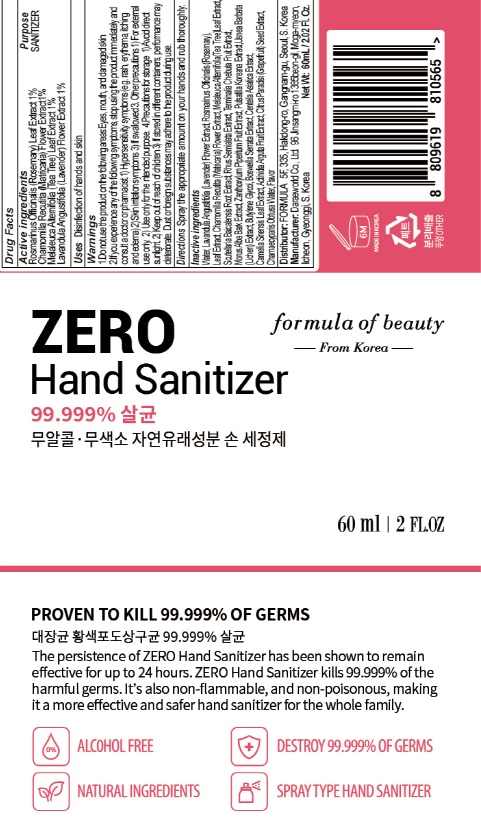 DRUG LABEL: ZERO Hand Sanitizer
NDC: 74772-010 | Form: LIQUID
Manufacturer: FORMULA
Category: otc | Type: HUMAN OTC DRUG LABEL
Date: 20200408

ACTIVE INGREDIENTS: ROSEMARY 1.0 g/100 mL; CHAMOMILE 1.0 g/100 mL; MELALEUCA ALTERNIFOLIA LEAF 1.0 g/100 mL; LAVANDULA ANGUSTIFOLIA SUBSP. ANGUSTIFOLIA FLOWER 1.0 g/100 mL
INACTIVE INGREDIENTS: Water; Butylene Glycol

ACTIVE INGREDIENT

Active ingredients:
Rosmarinus Officinalis (Rosemary) Leaf Extract 1%
Chamomilla Recutita (Matricaria) Flower Extract1%
Melaleuca Alternifolia (Tea Tree) Leaf Extract 1%
Lavandula Angustifolia (Lavender) Flower Extract 1%

INACTIVE INGREDIENT

Inactive ingredients:

Water, Lavandula Angustifolia (Lavender) Flower Extract, Rosmarinus Officinalis (Rosemary) Leaf Extract, Chamomilla Recutita (Matricaria) Flower Extract, Melaleuca Alternifolia (Tea Tree) Leaf Extract, Scutellaria Baicalensis Root Extract, Rhus Semialata Extract, Terminalia Chebula Fruit Extract, Morus Alba Bark Extract, Zanthoxylum Piperitum Fruit Extract, Pulsatilla Koreana Extract, Usnea Barbata (Lichen) Extract, Butylene Glycol, Boswellia Serrata Extract, Centella Asiatica Extract, Camellia Sinensis Leaf Extract, Actinidia Arguta Fruit Extract, Citrus Paradisi (Grapefruit) Seed Extract, Chamaecyparis Obtusa Water, Flavor

PURPOSE

Purpose: SANITIZER

WARNINGS

1.Do not use the product on the following areas:
Eyes, mouth, and damaged skin (irritation may occur)
2.If you experience any of the following symptoms, stop using the product immediately and consult a doctor or pharmacist.
1) Hypersensitivity symptoms (e.g. rash, erythema, itching and edema)
2) Skin irritation symptoms
3. Other precautions
1) For external use only. (Do not swallow. If swallowed, vomit and consult a doctor or pharmacist)
2) Avoid contact with eyes. If in contact, wash with clean water and consult a doctor or pharmacist.
3) Do not use sealed bandages, cast bandages or packs as they may cause irritation.
4) Do not use this medicine for anal or vaginal areas or hot packs as it may cause irritation.
5) Use only for the intended purpose.
4.Precautions for storage
1) Keep away from direct sunlight and do not expose the product to heating devices or flame.
2) Keep out of reach of children and go to the hospital immediately if swallowed.
3) After use, close the lid completely to prevent the product from drying or foreign objects from getting inside the container.
4) Storing the product in a different container may cause accidents or deterioration of quality. Therefore, keep the product in its original container.
Dust or foreign substances may get on the product while using it.

Keep out of reach of children and go to the hospital immediately if swallowed.

Uses

Disinfection of hands and skin

Directions

Directions (for Gel type)

Take an appropriate amount on your hands and rub thoroughly to dry.

Directions (for Spray type)
Spray the appropriate amount on your hands and rub thoroughly.